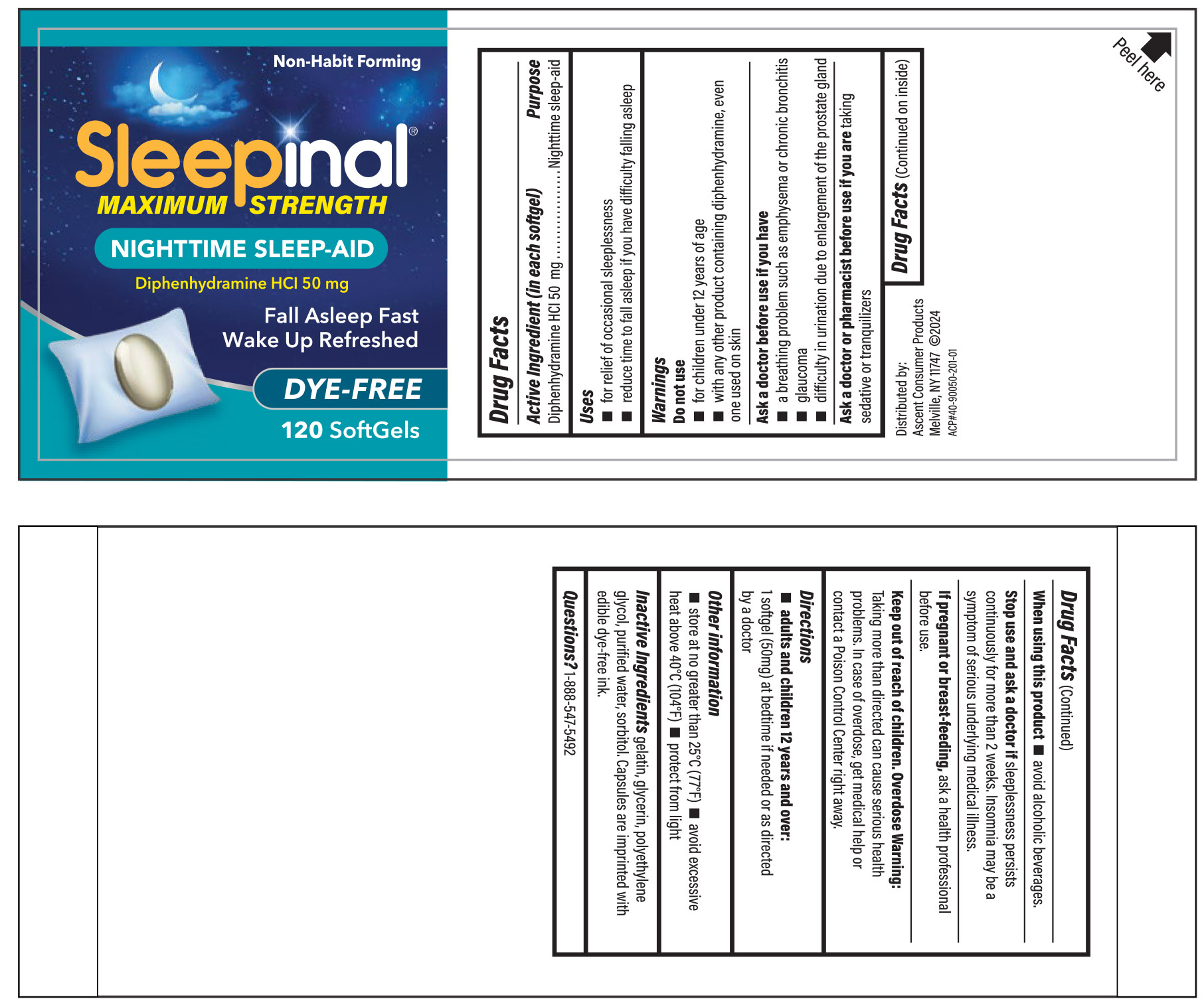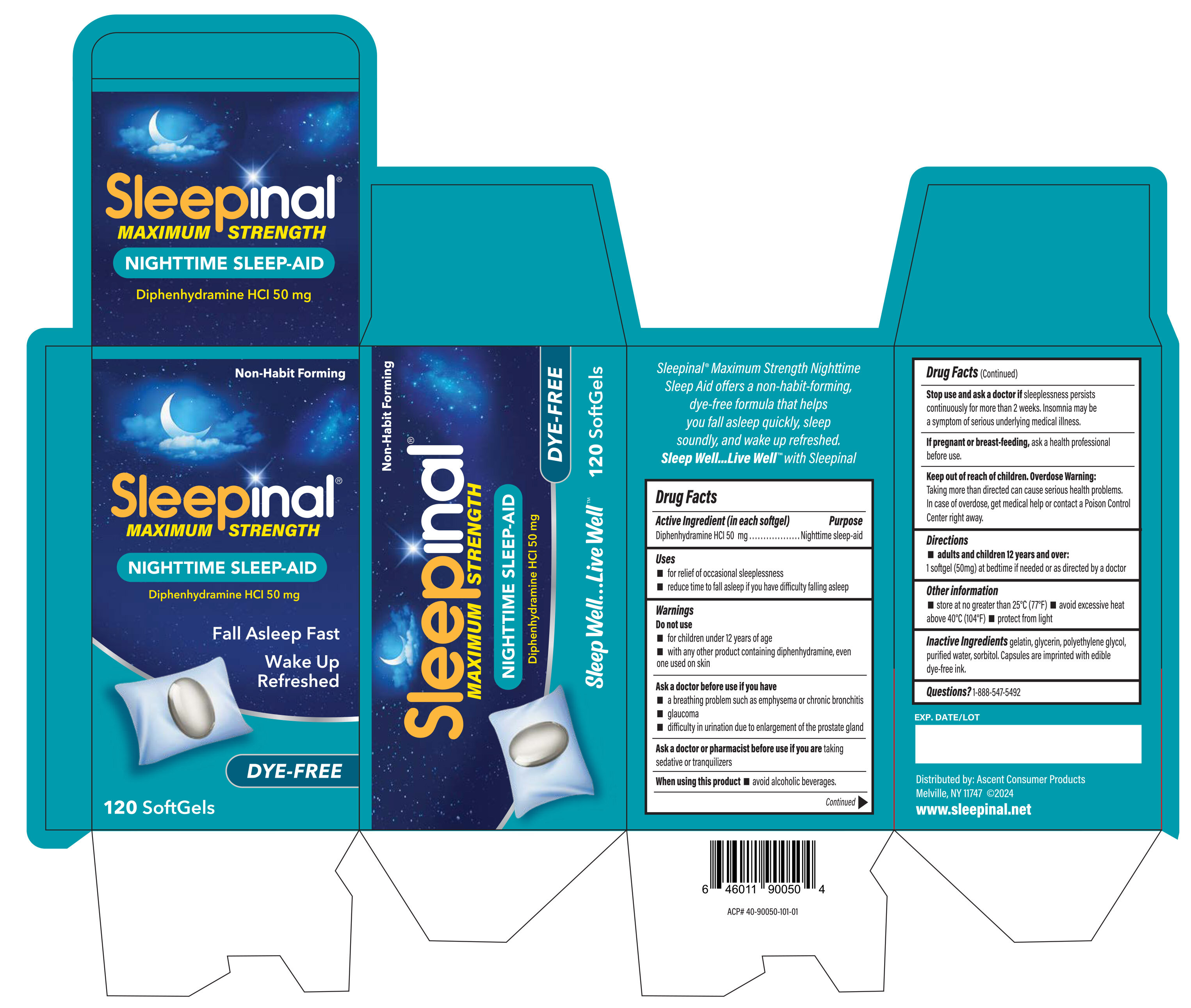 DRUG LABEL: Nighttime sleep aid
NDC: 42829-950 | Form: CAPSULE, LIQUID FILLED
Manufacturer: ASCENT CONSUMER PRODUCTS, INC
Category: otc | Type: HUMAN OTC DRUG LABEL
Date: 20250519

ACTIVE INGREDIENTS: DIPHENHYDRAMINE HYDROCHLORIDE 50 mg/1 1
INACTIVE INGREDIENTS: GELATIN, UNSPECIFIED; GLYCERIN; POLYETHYLENE GLYCOL, UNSPECIFIED; WATER; SORBITOL

Nighttime Sleep-Aid

Active ingredient (in each softgel)

Diphenhydramine HCl 50 mg

Purpose

Nighttime sleep-aid

Uses

- for the relief of occasional sleeplessness
- reduces time to fall asleep if you have difficulty falling asleep

Warnings

Do not use

for children under 12 years if age

with any other product containing diphenhydramine, even one used on skin

Ask a doctor before use if you have

a breathing problem such as emphysema or chronic bronchitis

glaucoma

difficulty in urniation due to enlargement of the prostate gland

Ask a doctor or pharmacist before use if you are

taking sedative or tranquilizers

When usiing this product avoid alcoholic beverages

Keep out of reach of children

Do not use

- for children under 12 years of age
- with any other product containing diphenhydramine, even one used on skin

Ask a doctor before use if you have

- a breathing problem such as emphysema or chronic bronchitis
- glaucoma
- difficulty in urination due to an enlargement of the prostate gland

Ask a doctor or pharmacist before use if you are

taking sedatives or tranquilizers

When using this product

- avoid alcoholic beverages

Stop use and ask a doctor if

sleeplessness persists continuously for more than 2 weeks. Insomnia may be a symptom of serious underlying medical illness.

If pregnant or breast-feeding,

ask a health professional before use.

Ask a doctor or pharmacist before use if you are

taking sedative or tranquilizers

Ask a doctor before use if you have

a breathing problem such as emphysema or chronic bronchitis

glaucoma

difficulty in urination due to enlargement of the prostate gland

if pregnant or breast feeding

ask a health professional before use

Keep out of reach of children.

In case of overdose, get medical help or contact a Poison Control Center right away (1-800-222-1222).

Directions

- take only one dose per day (24 hours)- see overdose warning

1. adults & children 12 yrs & over | 1 softgel(50mg) at bedtime if needed or as directed by a doctor

Other information

- store at 20-25°C (68-77°F)
- avoid excessive heat above 40oC (104oF)
- protect from light

Inactive ingredients

edible dye free ink, gelatin, glycerin, polyethylene glycol, purified water, sorbitol

Questions or comments?

1-800-719-9260

Questions ?

1-888-547-5492

Other Information- Storage

Store at no greater than 25 degree C

avoid excessive heat above 40 degree C

protect from light